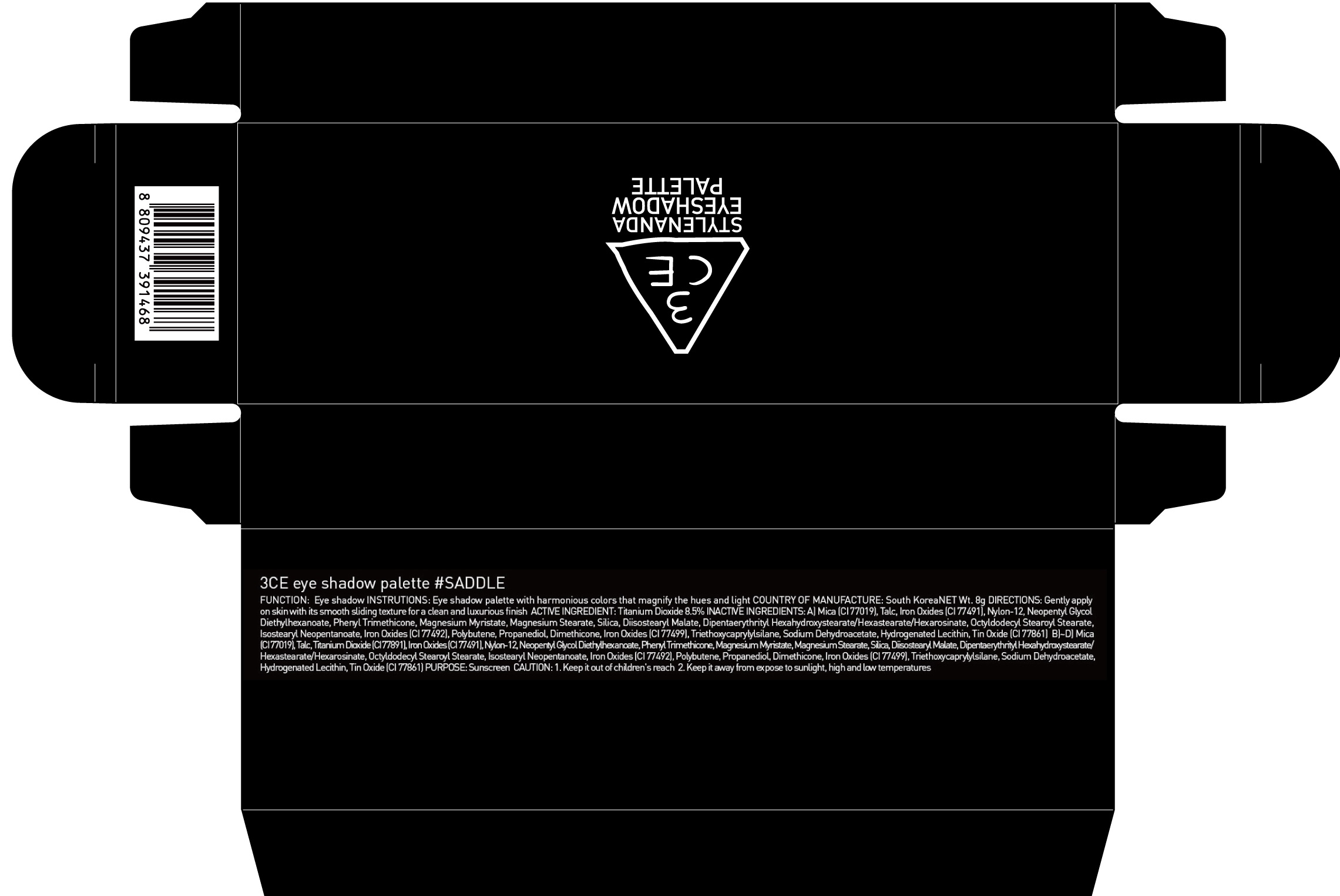 DRUG LABEL: 3CE EYE SHADOW PALETTE SADDLE
NDC: 60764-065 | Form: POWDER
Manufacturer: Nanda Co., Ltd
Category: otc | Type: HUMAN OTC DRUG LABEL
Date: 20161004

ACTIVE INGREDIENTS: Titanium Dioxide 0.68 g/8 g
INACTIVE INGREDIENTS: Mica; Talc

ACTIVE INGREDIENT

Active Ingredient: Titanium Dioxide 8.5%

INACTIVE INGREDIENT

Inactive Ingredients:

A) Mica (CI 77019), Talc, Iron Oxides (CI 77491), Nylon-12, Neopentyl Glycol Diethylhexanoate, Phenyl Trimethicone, Magnesium Myristate, Magnesium Stearate, Silica, Diisostearyl Malate, Dipentaerythrityl Hexahydroxystearate/Hexastearate/Hexarosinate, Octyldodecyl Stearoyl Stearate, Isostearyl Neopentanoate, Iron Oxides (CI 77492), Polybutene, Propanediol, Dimethicone, Iron Oxides (CI 77499), Triethoxycaprylylsilane, Sodium Dehydroacetate, Hydrogenated Lecithin, Tin Oxide (CI 77861)

B)~D) Mica (CI 77019), Talc, Titanium Dioxide (CI 77891), Iron Oxides (CI 77491), Nylon-12, Neopentyl Glycol Diethylhexanoate, Phenyl Trimethicone, Magnesium Myristate, Magnesium Stearate, Silica, Diisostearyl Malate, Dipentaerythrityl Hexahydroxystearate/Hexastearate/Hexarosinate, Octyldodecyl Stearoyl Stearate, Isostearyl Neopentanoate, Iron Oxides (CI 77492), Polybutene, Propanediol, Dimethicone, Iron Oxides (CI 77499), Triethoxycaprylylsilane, Sodium Dehydroacetate, Hydrogenated Lecithin, Tin Oxide (CI 77861)

PURPOSE

Purpose: Sunscreen

CAUTION

CAUTION: 1. Keep it out of children's reach 2. Keep it away from expose to sunlight, high and low temperatures.

DESCRIPTION

INSTRUCTIONS: Eye shadow palette with harmonious colors that magnify the hues and light.

Directions: Gently apply on skin with its smooth sliding texture for a clean and luxurious finish